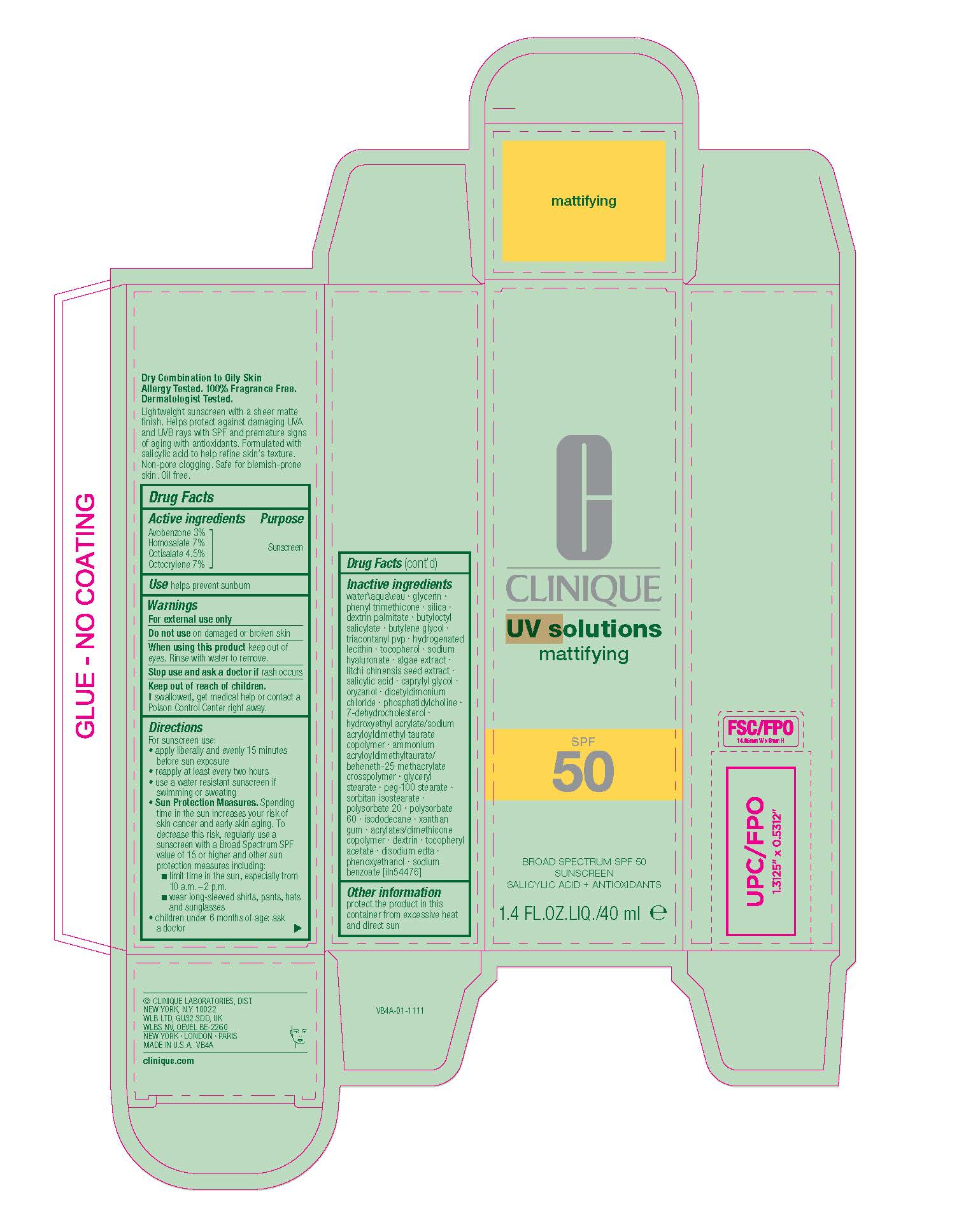 DRUG LABEL: UV SOLUTIONS MATTIFYING BROAD SPECTRUM SPF 50
NDC: 49527-226 | Form: CREAM
Manufacturer: CLINIQUE LABORATORIES LLC
Category: otc | Type: HUMAN OTC DRUG LABEL
Date: 20251020

ACTIVE INGREDIENTS: OCTISALATE 45 mg/1 mL; OCTOCRYLENE 70 mg/1 mL; AVOBENZONE 30 mg/1 mL; HOMOSALATE 70 mg/1 mL
INACTIVE INGREDIENTS: BUTYLENE GLYCOL; DEXTRIN PALMITATE (CORN; 20000 MW); HYDROGENATED SOYBEAN LECITHIN; TOCOPHEROL; PEG-100 STEARATE; ISODODECANE; HYDROXYETHYL ACRYLATE/SODIUM ACRYLOYLDIMETHYL TAURATE COPOLYMER (45000 MPA.S AT 1%); BUTYLOCTYL SALICYLATE; TRIACONTANYL PVP; SODIUM HYALURONATE; DEXTRIN, CORN; PHENOXYETHANOL; SORBITAN ISOSTEARATE; POLYSORBATE 20; ALPHA-TOCOPHEROL ACETATE; AMMONIUM ACRYLOYLDIMETHYLTAURATE/BEHENETH-25 METHACRYLATE CROSSPOLYMER (52000 MPA.S); SALICYLIC ACID; SILICA; GLYCINE MAX (SOYBEAN) OIL; GLYCERYL STEARATE; GLYCERIN; PHENYL TRIMETHICONE; DICETYLDIMONIUM CHLORIDE; EDETATE DISODIUM ANHYDROUS; SODIUM BENZOATE; PORPHYRIDIUM PURPUREUM; CAPRYLYL GLYCOL; 7-DEHYDROCHOLESTEROL; XANTHAN GUM; LITCHI CHINENSIS SEED; ORYZANOL; POLYSORBATE 60; WATER

UV SOLUTIONS MATTIFYING BROAD SPECTRUM SPF 50

Active ingredients

Avobenzone 3%
Homosalate 7%
Octisalate 4.5%

Octocrylene 7%

Purpose

Sunscreen

Use

helps prevent sunburn

Warnings

For external use only

Do not use

on damaged or broken skin

When using this product

keep out of eyes. Rinse with water to remove.

Stop use and ask a doctor if

rash occurs

Keep out of reach of children.

If swallowed, get medical help or contact a Poison Control Center right away.

Directions

For sunscreen use:
• apply liberally and evenly 15 minutes before sun exposure
• reapply at least every two hours
• use a water resistant sunscreen if swimming or sweating
• Sun Protection Measures. Spending time in the sun increases your risk of skin cancer and early skin aging. To decrease this risk, regularly use a sunscreen with a Broad Spectrum SPF value of 15 or higher and other sun protection measures including:
■ limit time in the sun, especially from 10 a.m.–2 p.m.
■ wear long-sleeved shirts, pants, hats and sunglasses
• children under 6 months of age: ask a doctor

Inactive Ingredients

water\aqua\eau,glycerin,phenyl trimethicone,silica,dextrin palmitate,butyloctyl salicylate,butylene glycol,triacontanyl pvp,hydrogenated lecithin,tocopherol,sodium hyaluronate,algae extract,litchi chinensis seed extract,salicylic acid,caprylyl glycol,oryzanol,dicetyldimonium chloride,phosphatidylcholine,7-dehydrocholesterol,hydroxyethyl acrylate/sodium acryloyldimethyl taurate copolymer,ammonium acryloyldimethyltaurate/beheneth-25 methacrylate crosspolymer,glyceryl stearate,peg-100 stearate,sorbitan isostearate,polysorbate 20,polysorbate 60,isododecane,xanthan gum,acrylates/dimethicone copolymer,dextrin,tocopheryl acetate,disodium edta,phenoxyethanol,sodium benzoate [iln54476]

Other information

protect the product in this container from excessive heat and direct sun

PACKAGE LABEL

CLINIQUE

UV solutoins mattifying

SPF 50

BRAOD SPECTRUM SPF 50
SUNSCREEN
SALICYLIC ACID + ANTIOXIDANTS

1.4 FL.OZ.LIQ./40 ml